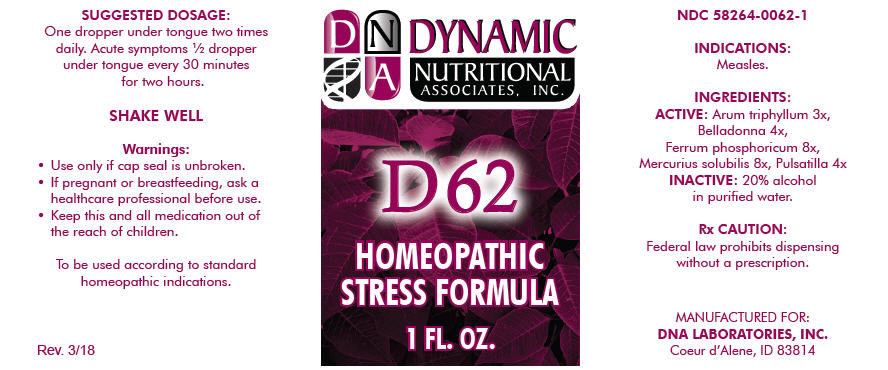 DRUG LABEL: D-62
NDC: 58264-0062 | Form: SOLUTION
Manufacturer: DNA Labs, Inc.
Category: homeopathic | Type: HUMAN OTC DRUG LABEL
Date: 20250113

ACTIVE INGREDIENTS: ARISAEMA TRIPHYLLUM ROOT 3 [hp_X]/1 mL; ATROPA BELLADONNA 4 [hp_X]/1 mL; FERROSOFERRIC PHOSPHATE 8 [hp_X]/1 mL; MERCURIUS SOLUBILIS 8 [hp_X]/1 mL; ANEMONE PRATENSIS 4 [hp_X]/1 mL
INACTIVE INGREDIENTS: ALCOHOL; WATER

D-62

NDC 58264-0062-1

INDICATIONS

PURPOSE

Measles.

INGREDIENTS

ACTIVE

Arum triphyllum 3x, Belladonna 4x, Ferrum phosphoricum 8x, Mercurius solubilis 8x, Pulsatilla 4x

INACTIVE

20% alcohol in purified water.

Rx CAUTION

Federal law prohibits dispensing without a prescription.

SUGGESTED DOSAGE

One dropper under tongue two times daily. Acute symptoms ½ dropper under tongue every 30 minutes for two hours.

STORAGE AND HANDLING

SHAKE WELL

Warnings

- Use only if cap seal is unbroken.

PREGNANCY OR BREAST FEEDING

- If pregnant or breastfeeding, ask a healthcare professional before use.

KEEP OUT OF REACH OF CHILDREN

- Keep this and all medication out of the reach of children.

To be used according to standard homeopathic indications.

PRINCIPAL DISPLAY PANEL - 1 FL. OZ. Bottle Label

DYNAMIC
NUTRITIONAL
ASSOCIATES, INC.

D 62

HOMEOPATHIC
STRESS FORMULA

1 FL. OZ.